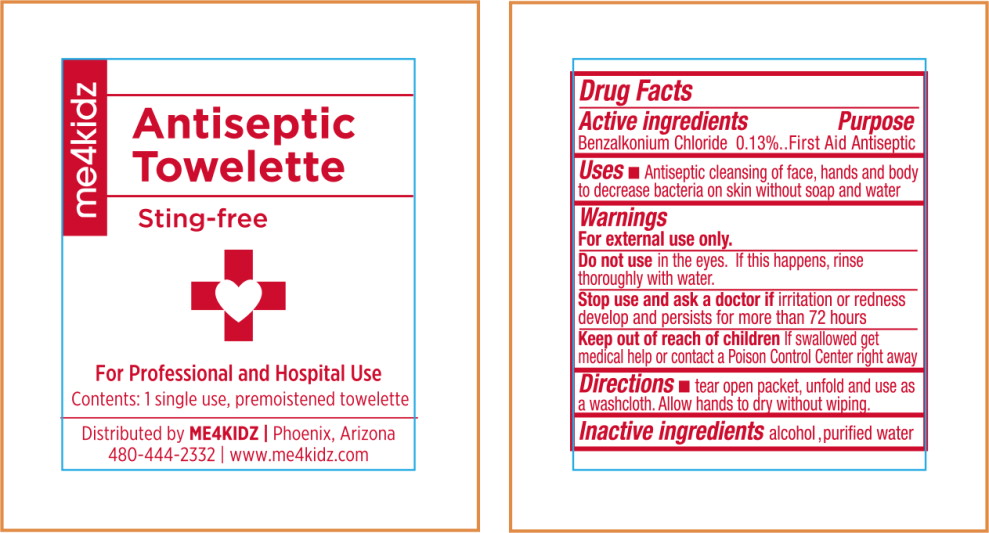 DRUG LABEL: BZK
NDC: 69535-413 | Form: LIQUID
Manufacturer: Me4Kids
Category: otc | Type: HUMAN OTC DRUG LABEL
Date: 20150115

ACTIVE INGREDIENTS: benzalkonium chloride 0.0013 g/1 g
INACTIVE INGREDIENTS: water; alcohol

Drug Facts

Active ingredients

Benzalkonium Chloride 0.13%

Purpose

First Aid Antiseptic

Uses

- Antiseptic cleansing of face, hands and body to decrease bacteria on skin without soap and water

Warnings

For external use only.

Do not use in the eyes' If this happens, rinse thoroughly with water.

Stop use and ask a doctor if irritation or redness develop and persists for more than 72 hours

Keep out of reach of children If swallowed get medical help or contact a Poison Control Center right away

Directions

- tear open packet unfold and use as a washcloth. Allow hands to dry without wiping.

Inactive ingredients

alcohol, purified water

Principal Display Panel - Packet Label

Antiseptic
Towelette

Sting-free

For Professional and Hospital Use

Contents: 1 single use, premoistened towelette

Distributed by ME4KIDZ | Phoenix, Arizona

480-444-2332 | www.me4kidz.com